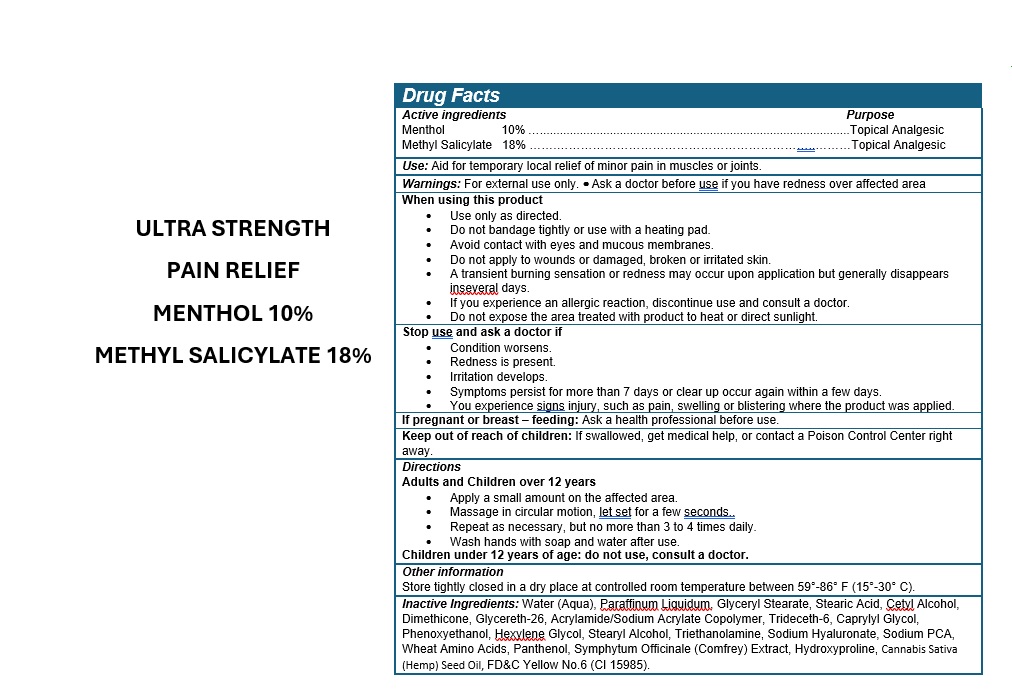 DRUG LABEL: HEATING PAIN RELIEF
NDC: 49283-579 | Form: CREAM
Manufacturer: CHEMCO CORPORATION
Category: otc | Type: HUMAN OTC DRUG LABEL
Date: 20260204

ACTIVE INGREDIENTS: MENTHOL 10 g/100 mL; METHYL SALICYLATE 18 g/100 mL
INACTIVE INGREDIENTS: GLYCERYL MONOSTEARATE; CETYL ALCOHOL; GLYCERETH-26; TRIDECETH-6; CAPRYLYL GLYCOL; PHENOXYETHANOL; COMFREY LEAF; CANNABIS SATIVA SEED OIL; WATER; HYALURONATE SODIUM; AMINO ACIDS, WHEAT; PANTHENOL; HYDROXYPROLINE; HEXYLENE GLYCOL; STEARIC ACID; DIMETHICONE 1000; STEARYL ALCOHOL; TROLAMINE; SODIUM PYRROLIDONE CARBOXYLATE; MINERAL OIL; FD&C YELLOW NO. 6

49283-579-20

ACTIVE INGREDIENT

Methyl Salicylate 18%

Menthol 10%

PURPOSE

Topical Analgesic.

Use

Aid for temporary local relief of minor pain in muscles or joints.

WARNINGS

For external use only. · Ask a doctor before use if you have redness over affected area

WHEN USING

Use only as directed
Do not bandage tightly or use with a heating pad
Avoid contact with eyes and mucous membranes
Do not apply to wounds or damaged, broken or irritated skin
If you experience an allergic reaction, discontinue use and consult a doctor.

Do not expose the area treated with product to heat or direct sunlight.

Stop use and ask a doctor if

Condition worsens
Redness is present
Irritation develops
Symptoms persist for more than 7 days or clear up occur again within a few days

You experience signs injury, such as pain, swelling or blistering where the product was applied.

If pregnant or breast-feeding

Ask a health professional before use.

KEEP OUT OF REACH OF CHILDREN

If swallowed, get medical help or contact a Poison Control Center right away.

Directions

Adults and Children over 12 years

Apply a small amount on the affected area.
Massage in circular motion, let set for a few seconds..
Repeat as necessary, but no more than 3 to 4 times daily.
Wash hands with soap and water after use.

Children under 12 years of age consult a doctor.

Other information

Store tightly closed in a dry place at controlled room temperature between 59°-86° F (15°-30° C).

INACTIVE INGREDIENT

Water (Aqua), Paraffinum Liquidum, Cetyl Alcohol, Glyceryl Stearate, Stearic Acid, Glycereth-26, Dimethicone, Acrylamide/Sodium Acrylate Copolymer, Trideceth-6, Caprylyl Glycol, Hexylene Glycol, Stearyl Alcohol, Triethanolamine, Sodium Hyaluronate, Sodium PCA, Wheat Amino Acids, Panthenol, Symphytum Officinale (Comfrey) Extract, Hydroxyproline, Cannabis Sativa (Hemp) Seed Oil, Phenoxyethanol, FD&C Yellow No.6 (CI 15985).